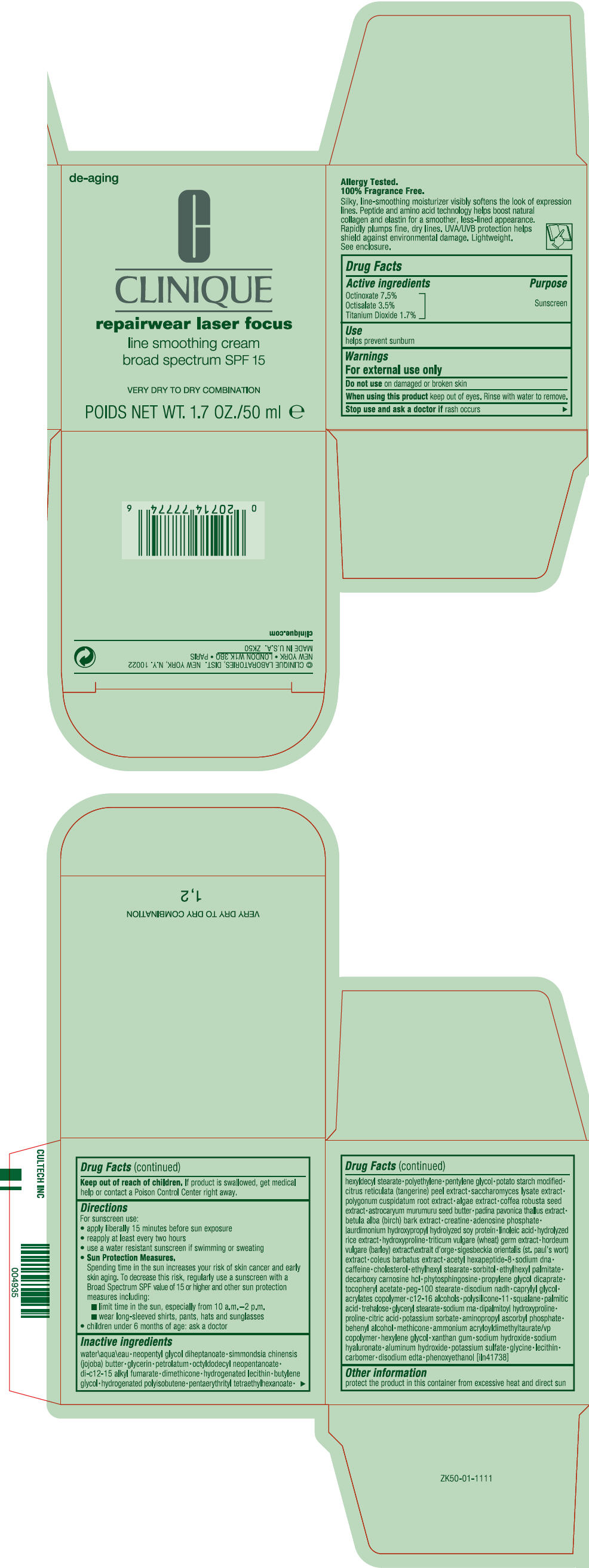 DRUG LABEL: REPAIRWEAR LASER FOCUS LINE SMOOTHING BROAD SPECTRUM SPF 15 -VERY DRY TO DRY COMBINATION
NDC: 49527-049 | Form: CREAM
Manufacturer: CLINIQUE LABORATORIES LLC
Category: otc | Type: HUMAN OTC DRUG LABEL
Date: 20231005

ACTIVE INGREDIENTS: OCTINOXATE 0.076125 g/100 mL; OCTISALATE 0.03745 g/100 mL; TITANIUM DIOXIDE 0.015225 g/100 mL
INACTIVE INGREDIENTS: WATER; NEOPENTYL GLYCOL DIHEPTANOATE; JOJOBA BUTTER; GLYCERIN; PETROLATUM; OCTYLDODECYL NEOPENTANOATE; DI-C12-15 ALKYL FUMARATE; DIMETHICONE; BUTYLENE GLYCOL; PENTAERYTHRITYL TETRAETHYLHEXANOATE; HEXYLDECYL STEARATE; HIGH DENSITY POLYETHYLENE; PENTYLENE GLYCOL; TANGERINE PEEL; SACCHAROMYCES LYSATE; REYNOUTRIA JAPONICA ROOT; ROBUSTA COFFEE BEAN; ASTROCARYUM MURUMURU SEED BUTTER; PADINA PAVONICA; BETULA PUBESCENS BARK; CREATINE; ADENOSINE PHOSPHATE; LINOLEIC ACID; HYDROXYPROLINE; WHEAT GERM; BARLEY; ACETYL HEXAPEPTIDE-8; CAFFEINE; CHOLESTEROL; ETHYLHEXYL STEARATE; SORBITOL; ETHYLHEXYL PALMITATE; DECARBOXY CARNOSINE HYDROCHLORIDE; PHYTOSPHINGOSINE; PROPYLENE GLYCOL DICAPRATE; .ALPHA.-TOCOPHEROL ACETATE; PEG-100 STEARATE; DISODIUM NICOTINAMIDE ADENINE DINUCLEOTIDE; CAPRYLYL GLYCOL; C12-16 ALCOHOLS; DIMETHICONE/VINYL DIMETHICONE CROSSPOLYMER (SOFT PARTICLE); SQUALANE; PALMITIC ACID; TREHALOSE; GLYCERYL MONOSTEARATE; DIPALMITOYL HYDROXYPROLINE; PROLINE; CITRIC ACID MONOHYDRATE; POTASSIUM SORBATE; AMINOPROPYL ASCORBYL PHOSPHATE; DOCOSANOL; AMMONIUM ACRYLOYLDIMETHYLTAURATE/VP COPOLYMER; HEXYLENE GLYCOL; XANTHAN GUM; SODIUM HYDROXIDE; HYALURONATE SODIUM; ALUMINUM HYDROXIDE; POTASSIUM SULFATE; GLYCINE; EDETATE DISODIUM; PHENOXYETHANOL

REPAIRWEAR LASER FOCUS LINE SMOOTHING CREAM BROAD SPECTRUM SPF 15 -VERY DRY TO DRY COMBINATION

Drug Facts

Active ingredients

Octinoxate 7.5%
Octisalate 3.5%
Titanium Dioxide 1.7%

Purpose

Sunscreen

Use

helps prevent sunburn

Warnings

For external use only

Do not use on damaged or broken skin

When using this product keep out of eyes. Rinse with water to remove.

Stop use and ask a doctor if rash occurs

Keep out of reach of children. If product is swallowed, get medical help or contact a Poison Control Center right away.

Directions

For sunscreen use:

- apply liberally 15 minutes before sun exposure
- reapply at least every two hours
- use a water resistant sunscreen if swimming or sweating
- Sun Protection Measures.
  Spending time in the sun increases your risk of skin cancer and early skin aging. To decrease this risk, regularly use a sunscreen with a Broad Spectrum SPF value of 15 or higher and other sun protection measures including:
  - limit time in the sun, especially from 10 a.m.–2 p.m.
  - wear long-sleeved shirts, pants, hats and sunglasses
- children under 6 months of age: ask a doctor

Inactive ingredients

water\aqua\eau • neopentyl glycol diheptanoate • simmondsia chinensis (jojoba) butter • glycerin • petrolatum • octyldodecyl neopentanoate • di-c12-15 alkyl fumarate • dimethicone • hydrogenated lecithin • butylene glycol • hydrogenated polyisobutene • pentaerythrityl tetraethylhexanoate • hexyldecyl stearate • polyethylene • pentylene glycol • potato starch modified • citrus reticulata (tangerine) peel extract • saccharomyces lysate extract • polygonum cuspidatum root extract • algae extract • coffea robusta seed extract • astrocaryum murumuru seed butter • padina pavonica thallus extract • betula alba (birch) bark extract • creatine • adenosine phosphate • laurdimonium hydroxypropyl hydrolyzed soy protein • linoleic acid • hydrolyzed rice extract • hydroxyproline • triticum vulgare (wheat) germ extract • hordeum vulgare (barley) extract\extrait d'orge • sigesbeckia orientalis (st. paul's wort) extract • coleus barbatus extract • acetyl hexapeptide-8 • sodium dna • caffeine • cholesterol • ethylhexyl stearate • sorbitol • ethylhexyl palmitate • decarboxy carnosine hcl • phytosphingosine • propylene glycol dicaprate • tocopheryl acetate • peg-100 stearate • disodium nadh • caprylyl glycol • acrylates copolymer • c12-16 alcohols • polysilicone-11 • squalane • palmitic acid • trehalose • glyceryl stearate • sodium rna • dipalmitoyl hydroxyproline • proline • citric acid • potassium sorbate • aminopropyl ascorbyl phosphate • behenyl alcohol • methicone • ammonium acryloyldimethyltaurate/vp copolymer • hexylene glycol • xanthan gum • sodium hydroxide • sodium hyaluronate • aluminum hydroxide • potassium sulfate • glycine • lecithin • carbomer • disodium edta • phenoxyethanol [iln41738]

Other information

protect the product in this container from excessive heat and direct sun

PRINCIPAL DISPLAY PANEL - 50 ml Jar Carton

de-aging

C
CLINIQUE

repairwear laser focus

line smoothing cream
broad spectrum SPF 15

VERY DRY TO DRY COMBINATION

POIDS NET WT. 1.7 OZ./50 ml e